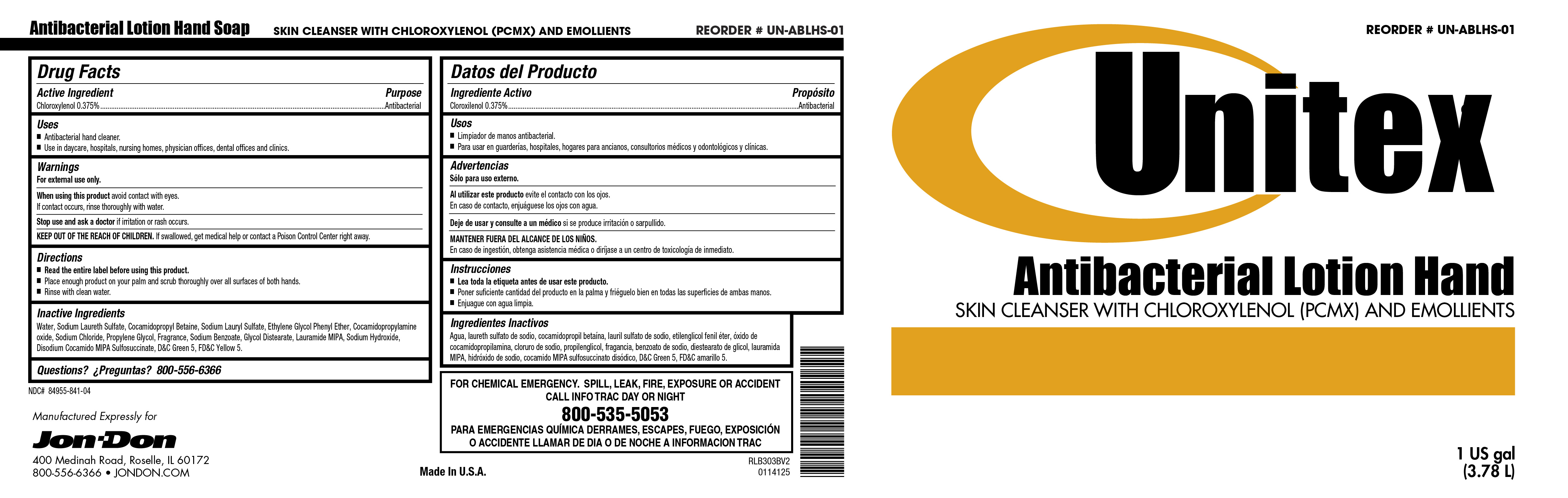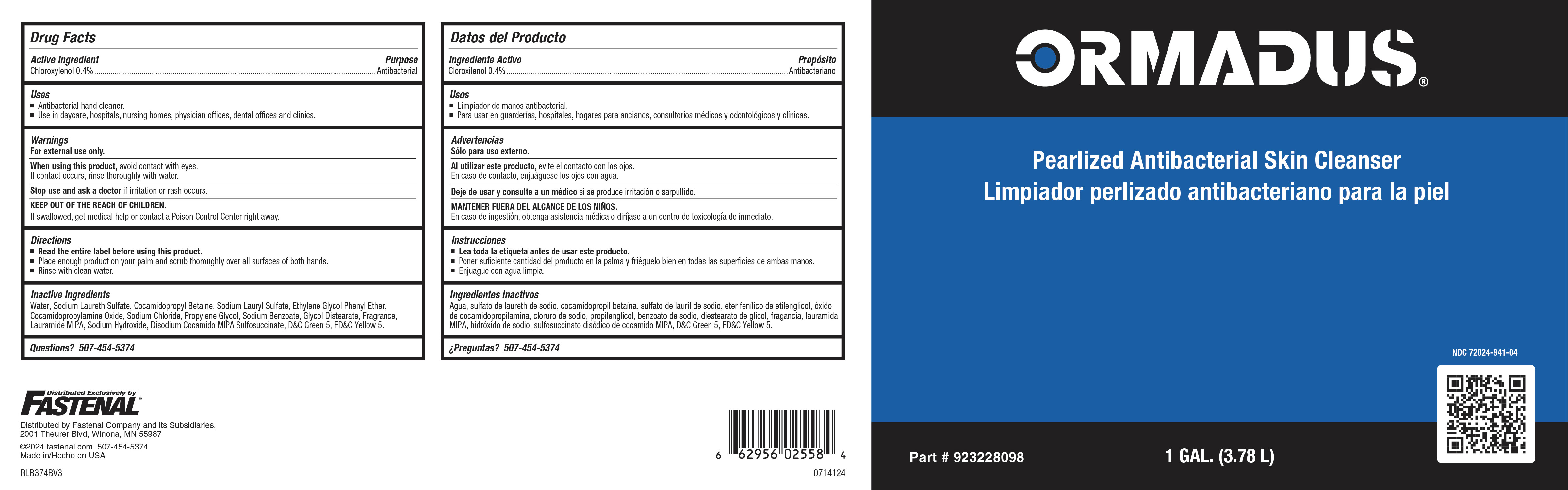 DRUG LABEL: Unitex Antibacterial LotionHandSoap
NDC: 84955-841 | Form: LIQUID
Manufacturer: Jon-Don  LLC
Category: otc | Type: HUMAN OTC DRUG LABEL
Date: 20241219

ACTIVE INGREDIENTS: CHLOROXYLENOL 4 mg/1 mL
INACTIVE INGREDIENTS: .ALPHA.-AMYLCINNAMALDEHYDE; .BETA.-CITRONELLOL, (+/-)-; 3-(3,4-METHYLENEDIOXYPHENYL)-2-METHYLPROPANAL; 4-ACETOXY-3-PENTYLTETRAHYDROPYRAN; SODIUM BENZOATE; 2-ISOBUTYL-4-METHYLTETRAHYDROPYRAN-4-OL; BENZYL SALICYLATE; 2-TERT-BUTYLCYCLOHEXYL ACETATE; HEXYL SALICYLATE; .GAMMA.-UNDECALACTONE; SODIUM CHLORIDE; D&C GREEN NO. 5; FD&C YELLOW NO. 5; LAURIC ISOPROPANOLAMIDE; SODIUM CARBONATE; GLYCOL DISTEARATE; SODIUM HYDROXIDE; CALCIUM SILICATE; SODIUM LAURYL SULFATE; LINALOOL, (+/-)-; TRIBASIC CALCIUM PHOSPHATE; SODIUM ALUMINIUM SILICATE; WATER; SODIUM LAURETH SULFATE; COCAMIDOPROPYL BETAINE; PHENOXYETHANOL; PROPYLENE GLYCOL; COCAMIDOPROPYLAMINE OXIDE; BENZYL ACETATE; .ALPHA.-HEXYLCINNAMALDEHYDE; 1-(2,3,8,8-TETRAMETHYL-1,2,3,4,5,6,7,8-OCTAHYDRONAPHTHALEN-2-YL)ETHANONE; DIHYDROMYRCENOL; HEXAHYDRO-4,7-METHANOINDEN-6-YL PROPIONATE; VERDYL ACETATE

Unitex Antibacterial Lotion Hand Soap

Active Ingredient

Chloroxylenol 0.40%

Uses

- Antibacterial hand cleaner.
- Use in daycare, hospitals, nursing homes, physicians offices, dental offices and clinics

Warnings

- For external use only.
- Avoid contact with eyes.
- Children under the age of 6 should be supervised by an adult when using this product.
- Discontinue use is irritation or redness develops.
- If irritation persists for more than 72 hours, consult a physician.
- KEEP OUT OF REACH OF CHILDREN.
- If swallowed, get medical help or contact a Poison Control Center right away.

Directions

- Read the entire label before using this product.
- Dispense 2 pumps of product onto palm of hand and scrub thoroughly over all surfaces of both hands.
- Rinse with clean water.

Inactive Ingredients

Water, Sodium Laureth lSulfate, Cocamidopropyl betadine, Phenoxyethanol, Coco MIPA, Glycol Stearate, DMDM Hydantoin, Propylene Glycol, Sodium Chloride, Fragrance, Glycerin, Ethanol, D&C Green #5, FD&C Yellow #5.

Purpose

Antibacterial

KEEP OUT OF REACH OF CHILDREN

Winning Hands Antibacterial

KEEP OUT OF REACH OF CHILDREN

©2017 Betco Corporation
400 Van Camp Road Bowling Green, Ohio 43402
Made In U.S.A. All Rights Reserved.

888-GO BETCO (888-462-3826) | Betco.com